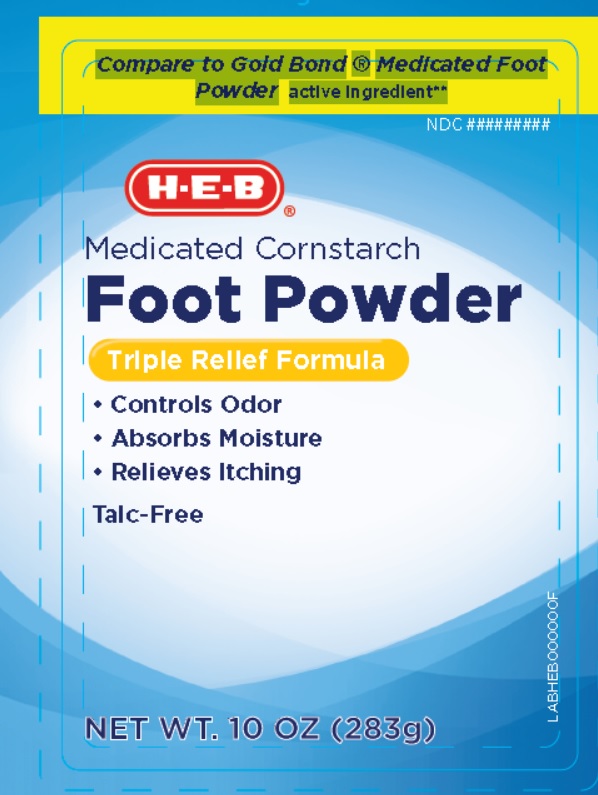 DRUG LABEL: H-E-B Medicated Corn Starch Foot Powder
NDC: 42669-218 | Form: POWDER
Manufacturer: Davion, Inc
Category: otc | Type: HUMAN OTC DRUG LABEL
Date: 20251229

ACTIVE INGREDIENTS: MENTHOL 1 g/100 g
INACTIVE INGREDIENTS: STARCH, CORN; TRICALCIUM PHOSPHATE; SODIUM BICARBONATE; BENZETHONIUM CHLORIDE; EUCALYPTUS OIL; PEPPERMINT OIL

H-E-B Medicated Corn Starch Foot Powder

Active Ingredient

Menthol 1.0%

Purpose

External Analgesic

Uses

Temporary relief of pain and itch associate with:

- Minor Cuts
- Sunburn
- Insect Bites
- Scrapes
- Minor Burns
- Minor Skin Irritations

Warnings

- For external use only
- Avoid contact with eyes

Stop use and ask a doctor if

- Condition worsens
- Symptoms persist for more than 7 days or clear up and occur again within few days

Keep out of reach of children

In case of accidental ingestion, get medical help or contact a Poison Control Center right away.

Directions

- Adults and children 2 years and older - Apply freely upto 3 or 4 times daily
- Children under 2 years - Ask a doctor
- For best results, dry skin throughly before applying

Inactive ingredients

Zea Mays (Corn) Starch, Tricalcium Phosphate, Sodium Bicarbonate, Benzethonium Chloride, Eucalyptus Oil, Peppermint Oil.

PRINCIPAL DISPLAY PANEL

NDC 42669-218-10

Compare to Gold Bond ® Medicated Foot Powder active ingredient*

H-E-B Medicated Corn Starch Foot Powder

TRIPLE RELIEF FORMULA

- Controls Odor
- Absorbs Moisture
- Relieves Itching

Talc-Free

NET WT. 10 OZ (283g)